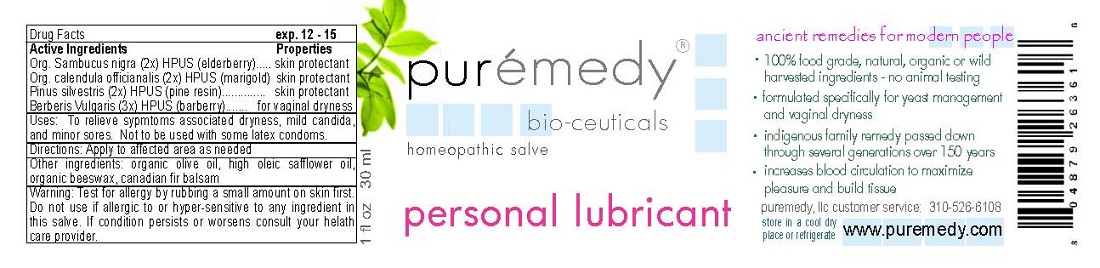 DRUG LABEL: PERSONAL LUBRICANT
NDC: 52810-801 | Form: SALVE
Manufacturer: PUREMEDY
Category: homeopathic | Type: HUMAN OTC DRUG LABEL
Date: 20211006

ACTIVE INGREDIENTS: SAMBUCUS NIGRA FLOWER 2 [hp_X]/100 mL; CALENDULA OFFICINALIS FLOWER 2 [hp_X]/100 mL; PINE NEEDLE OIL (PINUS SYLVESTRIS) 2 [hp_X]/100 mL; BERBERIS VULGARIS FRUIT 3 [hp_X]/100 mL
INACTIVE INGREDIENTS: OLIVE OIL; SAFFLOWER OIL; YELLOW WAX; CANADA BALSAM

PERSONAL LUBRICANT (52810-801)

ACTIVE INGREDIENTS

ORG. SAMBUCUS NIGRA (2X) HPUS (ELDERBERRY)

ORG. CALENDULA OFFICINALIS (2X) HPUS) (MARIGOLD)

PINUS SILVESTRIS (2X) HPUS (PINE RESIN)

BERBERIS VULGARIS (3X) HPUS (BARBERRY)

PURPOSE

PROPERTIES

SKIN PROTECTANT

SKIN PROTECTANT

SKIN PROTECTANT

FOR VAGINAL DRYNESS

INDICATIONS AND USAGE

USES: TO RELIEVE SYMPTOMS ASSOCIATED WITH DRYNESS, MILD CANDIDA, AND MINOR SORES. NOT TO BE USED SOME LATEX CONDOMS.

DOSAGE AND ADMINISTRATION

DIRECTIONS: APPLY TO AFFECTED AREA AS NEEDED.

INACTIVE INGREDIENT

OTHER INGREDIENTS: ORGANIC OLIVE OIL, HIGH OLEIC SAFFLOWER OIL, ORGANIC BEESWAX, CANADIAN FIR BALSAM

WARNINGS

WARNING: TEST FOR ALLERGY BY RUBBING A SMALL AMOUNT ON SKIN FIRST. DO NOT USE IF ALLERGIC TO OR HYPER-SENSITIVE TO ANY INGREDIENT IN THIS SALVE. IF CONDITION PERSISTS OR WORSENS CONSULT YOUR HEALTH CARE PROVIDER. (* = CERTIFIED ORGANIC INGREDIENTS)

KEEP OUT OF REACH OF CHILDREN.

QUESTIONS

CUSTOMER SERVICE 310-526-6108

OTHER SAFETY INFORMATION

STORE IN A COOL DRY PLACE OR REFRIGERATE